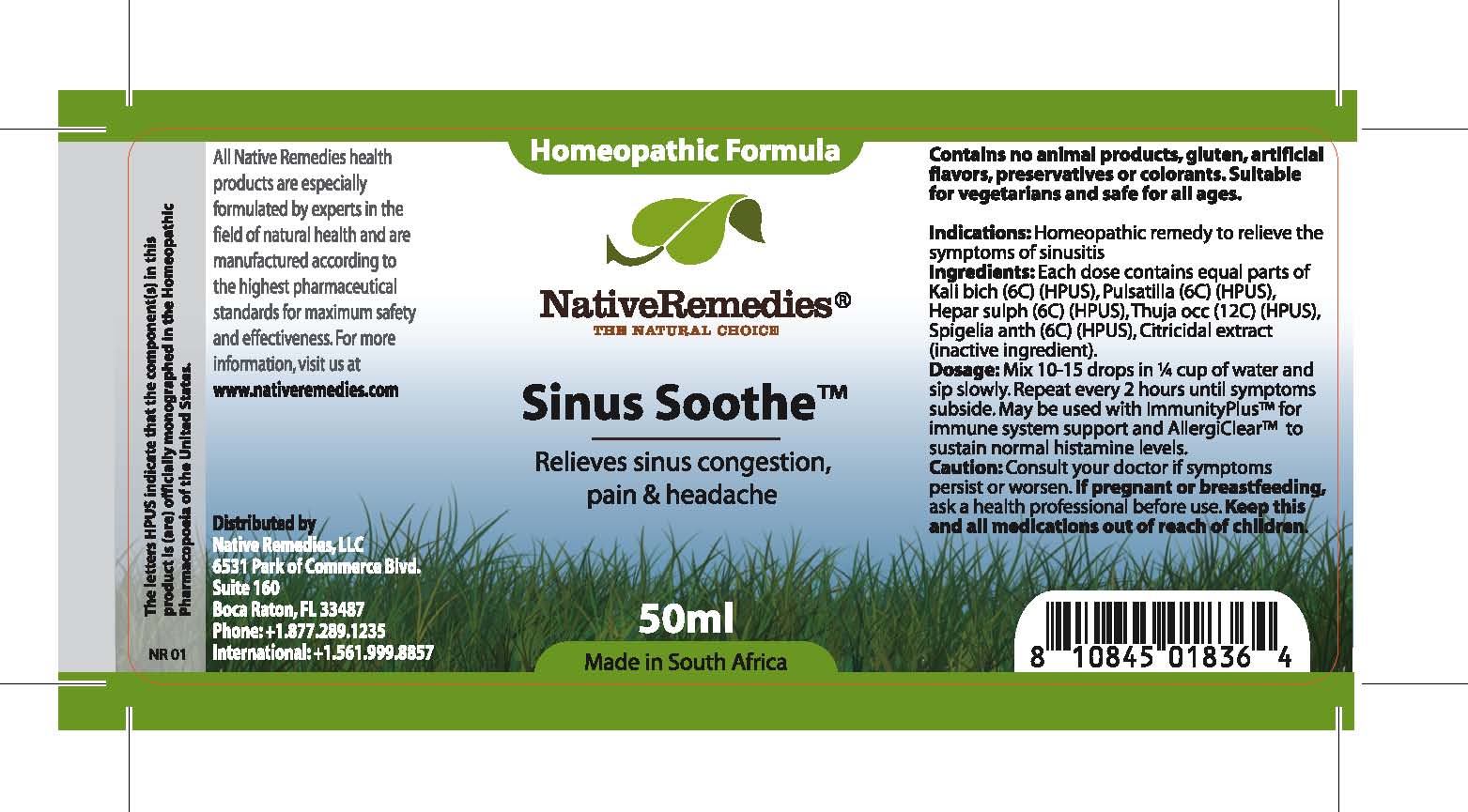 DRUG LABEL: Sinus Soothe
NDC: 68647-206 | Form: TINCTURE
Manufacturer: Feelgood Health
Category: homeopathic | Type: HUMAN OTC DRUG LABEL
Date: 20100817

ACTIVE INGREDIENTS: POTASSIUM DICHROMATE 6 [hp_C]/40 mL; PULSATILLA PATENS 6 [hp_C]/40 mL; CALCIUM SULFIDE 6 [hp_C]/40 mL; CEDAR LEAF OIL 12 [hp_C]/40 mL; SPIGELIA 6 [hp_C]/40 mL
INACTIVE INGREDIENTS: CITRUS PARADISI SEED 0.03 mL/50 mL; WATER 98.97 mL/50 mL

SINUS SOOTHE

PURPOSE

Relieves sinus congestion, pain and headache

INDICATIONS AND USAGE

Indications: Homeopathic remedy to relieve the symptoms of sinusitis

DOSAGE AND ADMINISTRATION

Dosage: Mix 10-15 drops in ¼ cup of water and sip slowly. Repeat every 2 hours until symptoms subside. May be used with ImmunityPlus™ for immune system support and AllergiClear™ to sustain normal histamine levels.

GENERAL PRECAUTIONS

Caution: Consult your doctor if symptoms persist or worsen. Keep this and all medications out of reach of children.

ACTIVE INGREDIENT

Ingredients: Each dose contains equal parts of Kali bich (6C) (HPUS), Pulsatilla (6C) (HPUS), Hepar sulph (6C) (HPUS), Thuja occ (12C) (HPUS), Spigelia anth (6C) (HPUS)

Citricidal extract (inactive ingredient).

PREGNANCY

If pregnant or breastfeeding, ask a health professional before use.

WARNINGS

Contains no animal products, gluten, artificial flavors, preservatives or colorants. Suitable for vegetarians and safe for all ages.

PATIENT COUNSELING INFORMATION

All Native Remedies health products are especially formulated by experts in the field of natural health and are manufactured according to the highest pharmaceutical standards for maximum safety and effectiveness. For more information, visit us at www.nativeremedies.com

Distributed by

Native Remedies, LLC

6531 Park of Commerce Blvd.

Suite 160

Boca Raton, FL 33487

Phone: 1.877.289.1235

International: + 1.561.999.8857

The letters HPUS indicate that the component(s) in this product is (are) officially monographed in the Homeopathic Pharmacopoeia of the United States.

KEEP OUT OF REACH OF CHILDREN

Keep this and all medications out of reach of children.